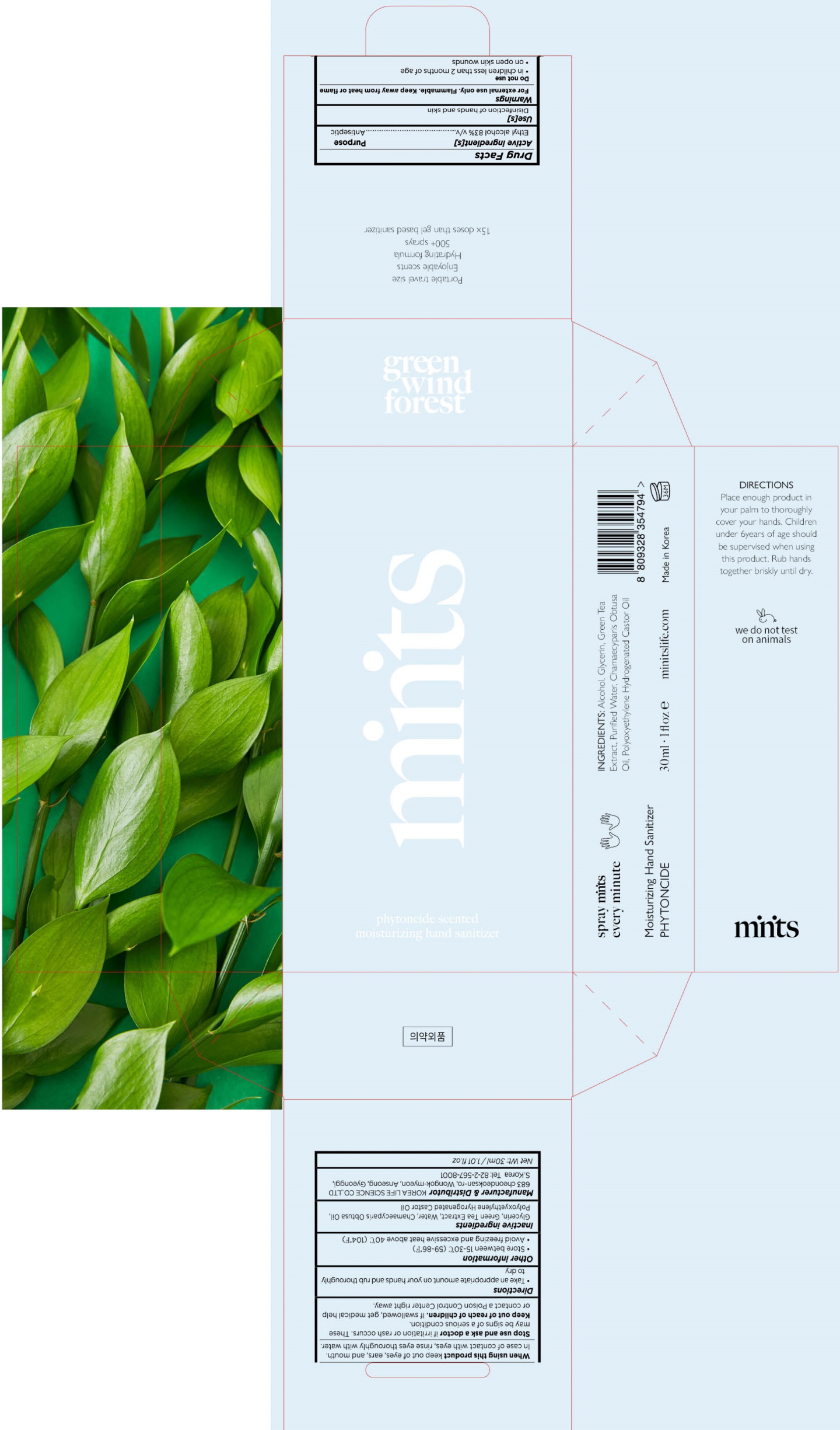 DRUG LABEL: Minits Hand Sanitizer
NDC: 74406-110 | Form: SPRAY
Manufacturer: Korea Life Science Co.,ltd
Category: otc | Type: HUMAN OTC DRUG LABEL
Date: 20200611

ACTIVE INGREDIENTS: ALCOHOL 24.9 mL/30 mL
INACTIVE INGREDIENTS: Water; CHAMAECYPARIS OBTUSA WOOD OIL; Glycerin; GREEN TEA LEAF

ACTIVE INGREDIENT

ETHANOL 83% w/w

INACTIVE INGREDIENTS

Water, Chamaecyparis Obtusa Oil, Glycerin, Polyoxyethylene Hydrogenated Castor Oil, Green Tea Extract

PURPOSE

ANTISEPTIC

WARNINGS

For external use only. Flammable. Keep away from heat or flame
--------------------------------------------------------------------------------------------------------
Do not use
• in children less than 2 months of age
• on open skin wounds
--------------------------------------------------------------------------------------------------------
When using this product keep out of eyes, ears, and mouth. In case of contact with eyes, rinse eyes thoroughly with water.
--------------------------------------------------------------------------------------------------------
Stop use and ask a doctor if irritation or rash occurs. These may be signs of a serious condition.

KEEP OUT OF REACH OF CHILDREN

If swallowed, get medical help or contact a Poison Control Center right away.

Uses

Disinfection of hands and skin

Directions

Take an appropriate amount on your hands and rub thoroughly to dry

Other information

• Store between 15-30C (59-86F)
• Avoid freezing and excessive heat above 40C (104F)